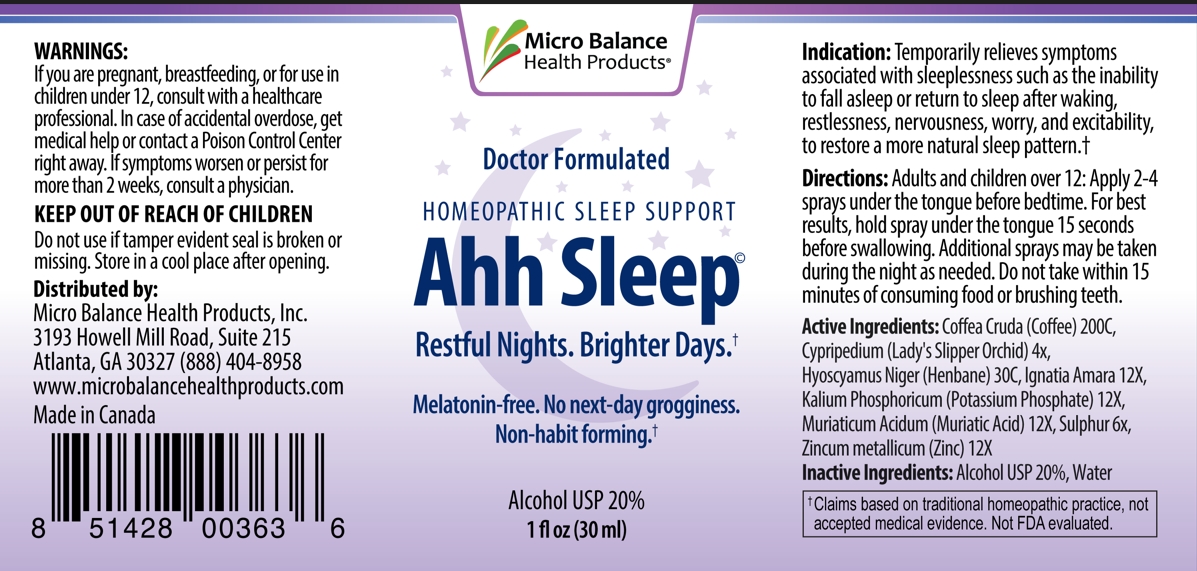 DRUG LABEL: Ahh Sleep
NDC: 83018-0004 | Form: SPRAY
Manufacturer: Micro Balance Health Products
Category: homeopathic | Type: HUMAN OTC DRUG LABEL
Date: 20231030

ACTIVE INGREDIENTS: CYPRIPEDIUM PARVIFLORUM VAR. PUBESCENS ROOT 4 [hp_X]/1 mL; HYDROCHLORIC ACID 12 [hp_X]/1 mL; ARABICA COFFEE BEAN 200 [hp_C]/1 mL; STRYCHNOS IGNATII SEED 12 [hp_X]/1 mL; ZINC 12 [hp_X]/1 mL; HYOSCYAMUS NIGER 30 [hp_C]/1 mL; SULFUR 6 [hp_X]/1 mL; POTASSIUM PHOSPHATE, UNSPECIFIED FORM 12 [hp_X]/1 mL
INACTIVE INGREDIENTS: ALCOHOL; WATER

Indication

Temporarily relieves symptoms associated with sleeplessness such as the inability to fall asleep or return to sleep after waking, restlessness, nervousness, worry, and excitability, to restore a more natural sleep pattern.

Directions

Adults and children over 12: Apply 2-4 sprays under the tongue before bedtime. For best results, hold spray under the tongue 15 seconds before swallow. Addtional sprays may be taken during the night as needed. Do not take within 15 minutes of consuming food or brushing teeth.

Active ingredients

Coffea cruda (coffee) 200 C；

Cypripedium (Lady's Slipper Orchid) 4x,

Hyoscyamus Niger (Henbane) 30C;

Ignatia Amara 12X;

Kalium Phosphoricum (Potassium Phosphate) 12X,

Muriaticum Acidum (Muriatic Acid) 12X;

Sulphur 6X;

Zincum Metallicum (Zinc) 12X

Inactive Ingredients

Alcohol USP 20%;

Water

Warnings

If you are pregnant, breastfeeding, or for use in children under 12, consult with a helthcare prefessional. In case of accidental overdose, get medical help or contact a Posion Control Center right away. If symptoms worsen or persist for more than 2 weeks, consult a physician.

PREGNANCY OR BREAST FEEDING

If you are pregnant, breastfeeding, or for use in children under 12, consult with a helthcare prefessional. In case of accidental overdose, get medical help or contact a Posion Control Center right away. If symptoms worsen or persist for more than 2 weeks, consult a physician.

Do not use if tamper evident seal is broken or missing. Store in a cool place after opening.

Keep out of reach of children

Micro balance Health Products

Doctor Formulated

Homeopathic Sleep Support

Ahh Sleep

Restful Nights, Brighter Days

Melationin-free. No next -day grogginess. Non-habit forming.

Alcohol USP20%

1 fl oz(30ml)

PURPOSE

Temporarily relieves symptoms associated with sleeplessness such as the inability to fall asleep or return to sleep after waking, restlessness, nervousness, worry, and excitability, to restore a more natural sleep pattern.